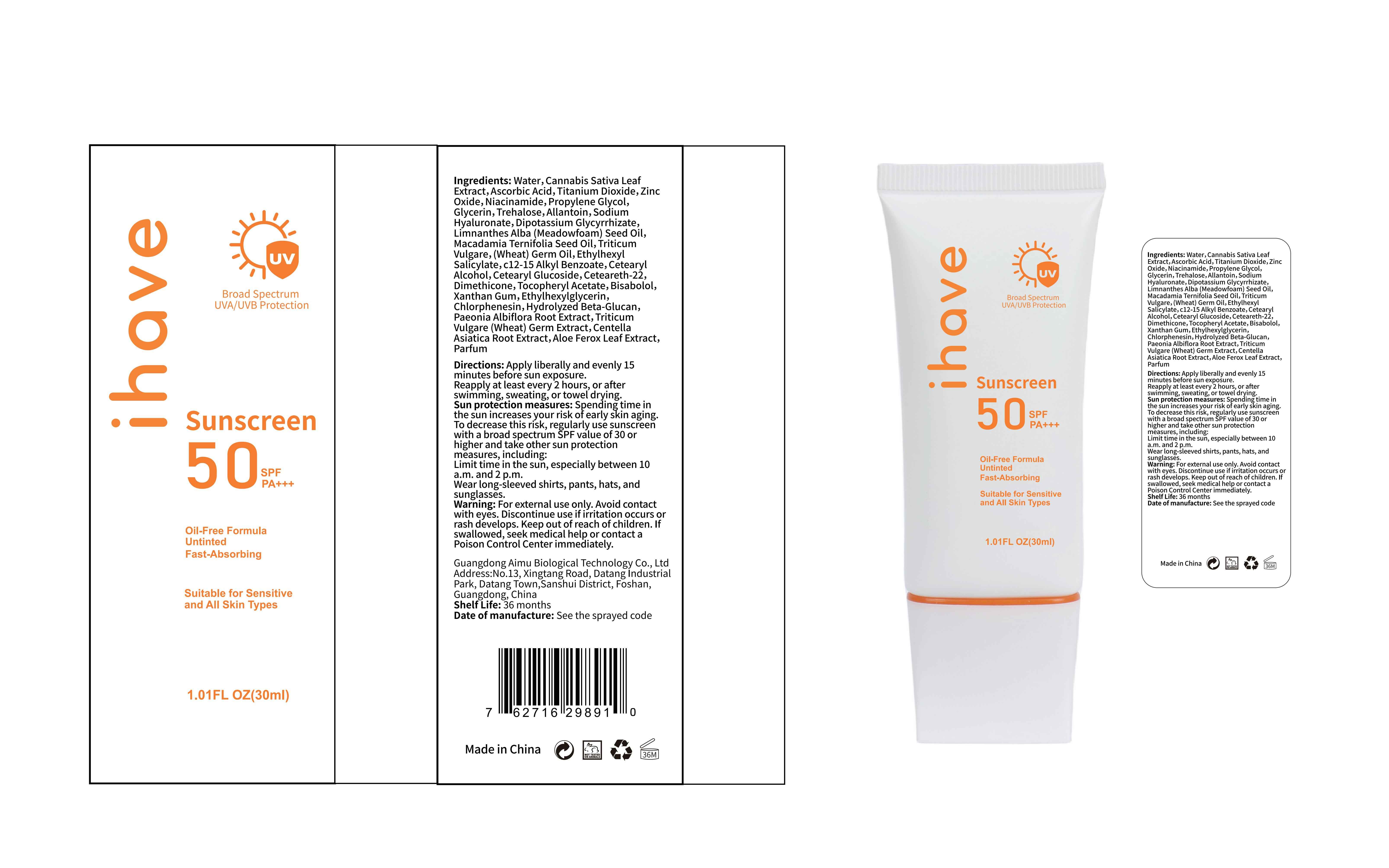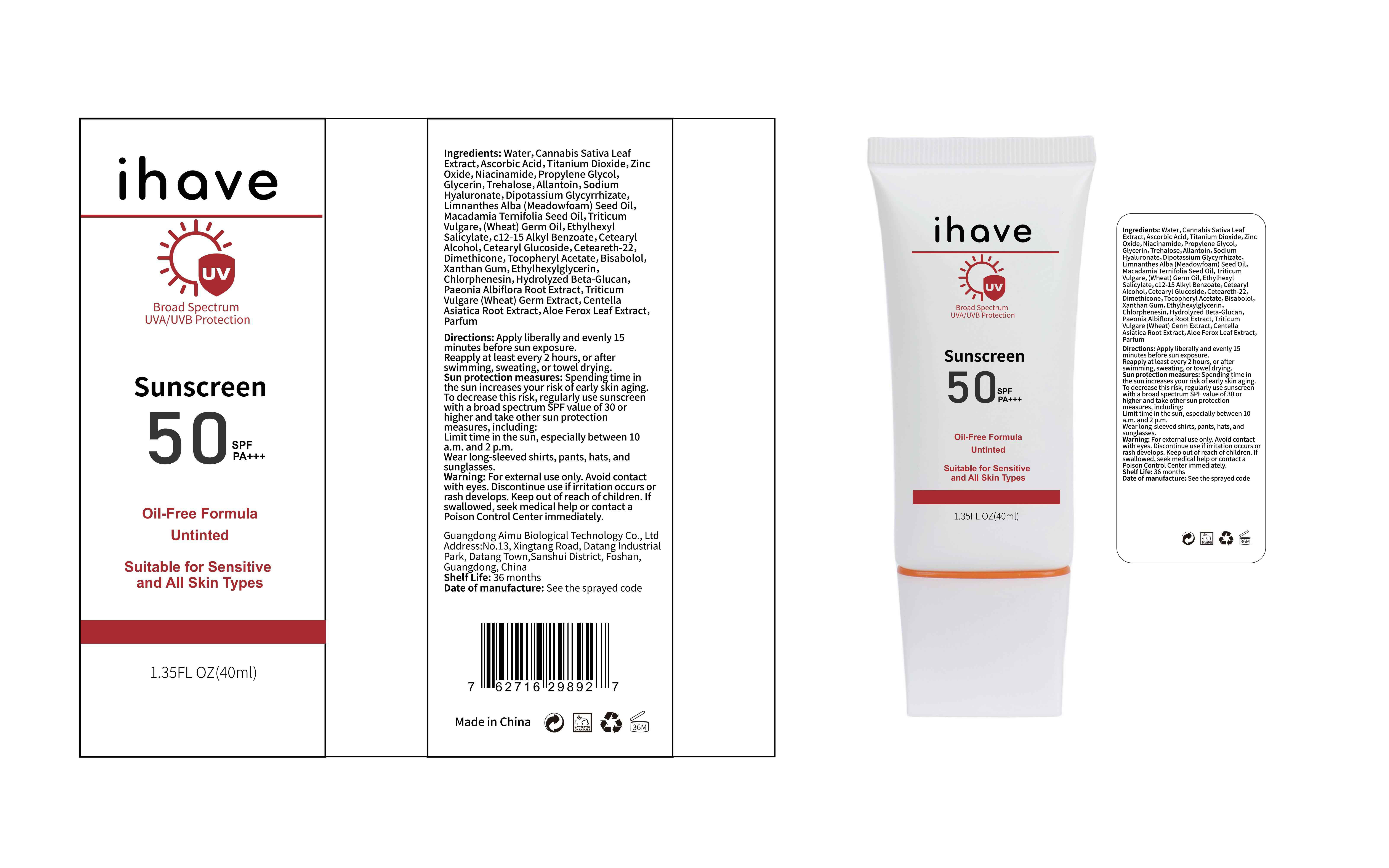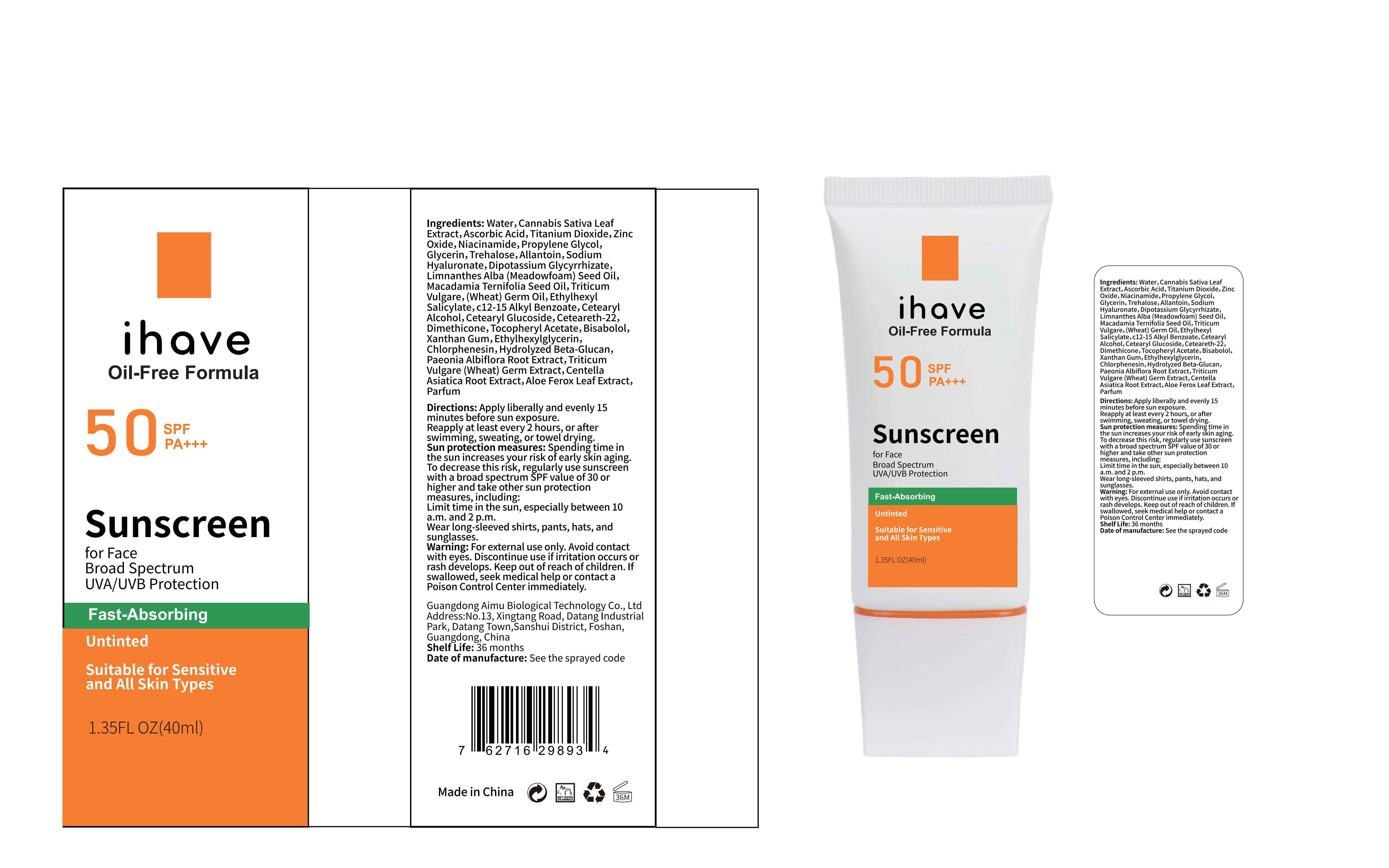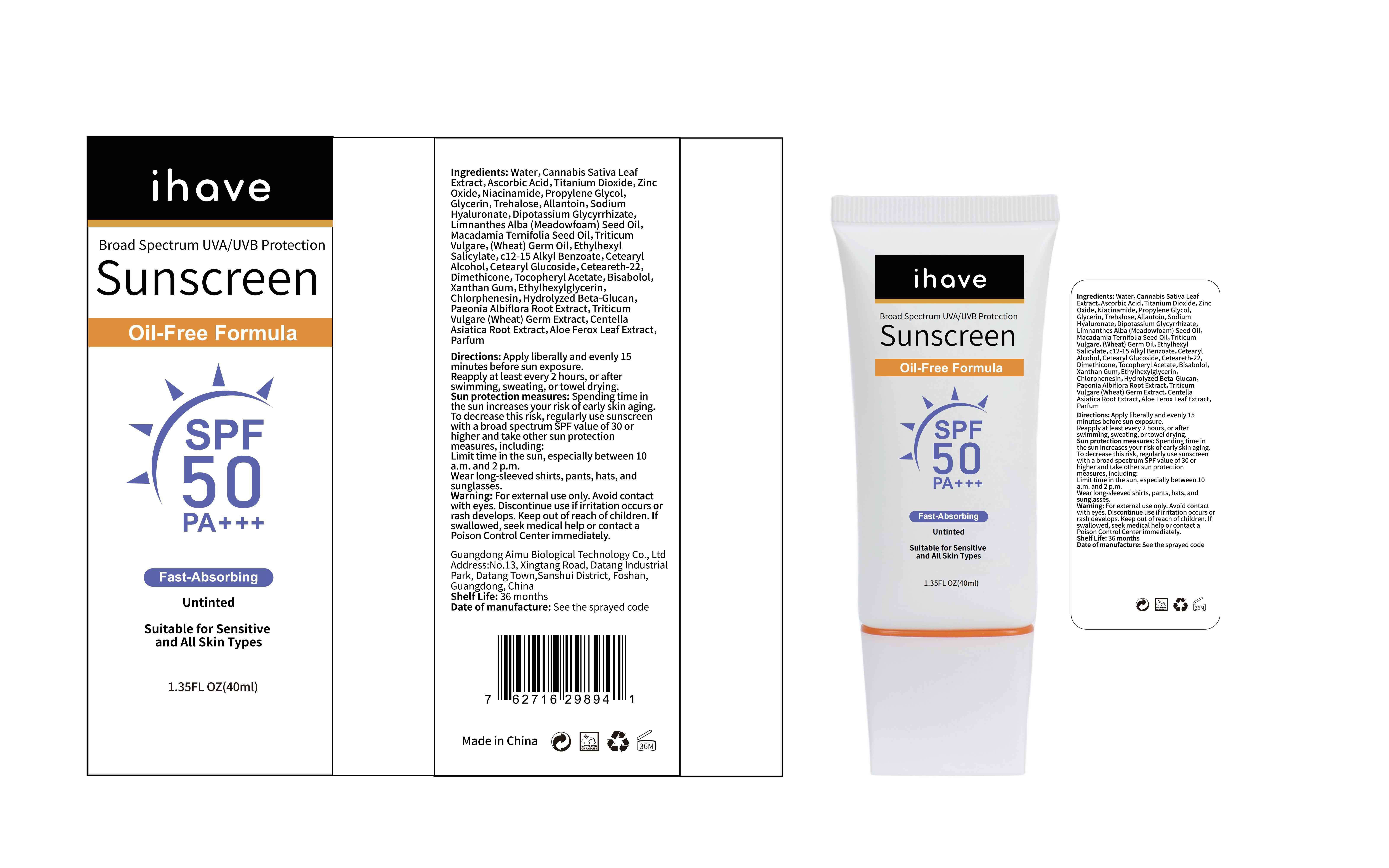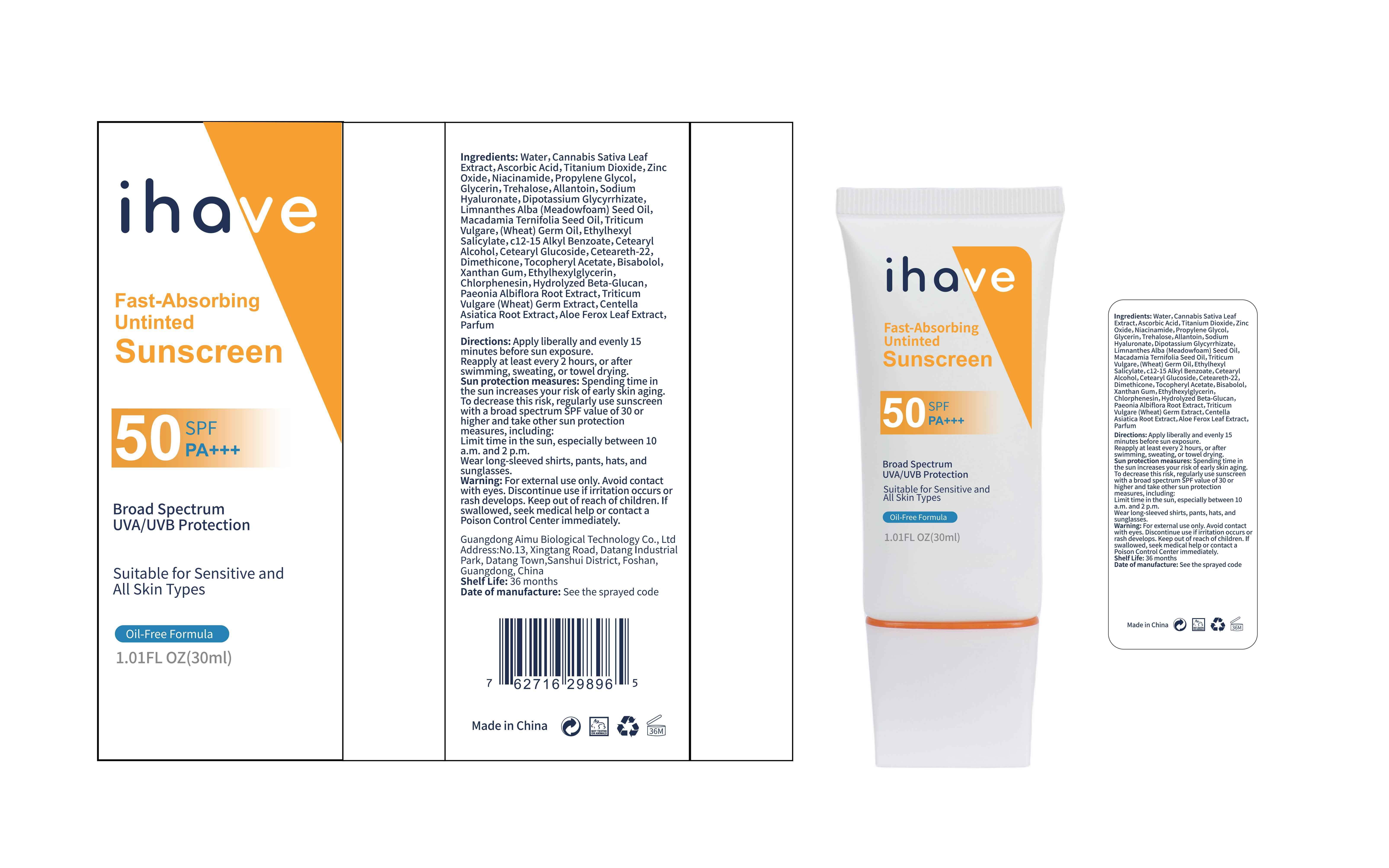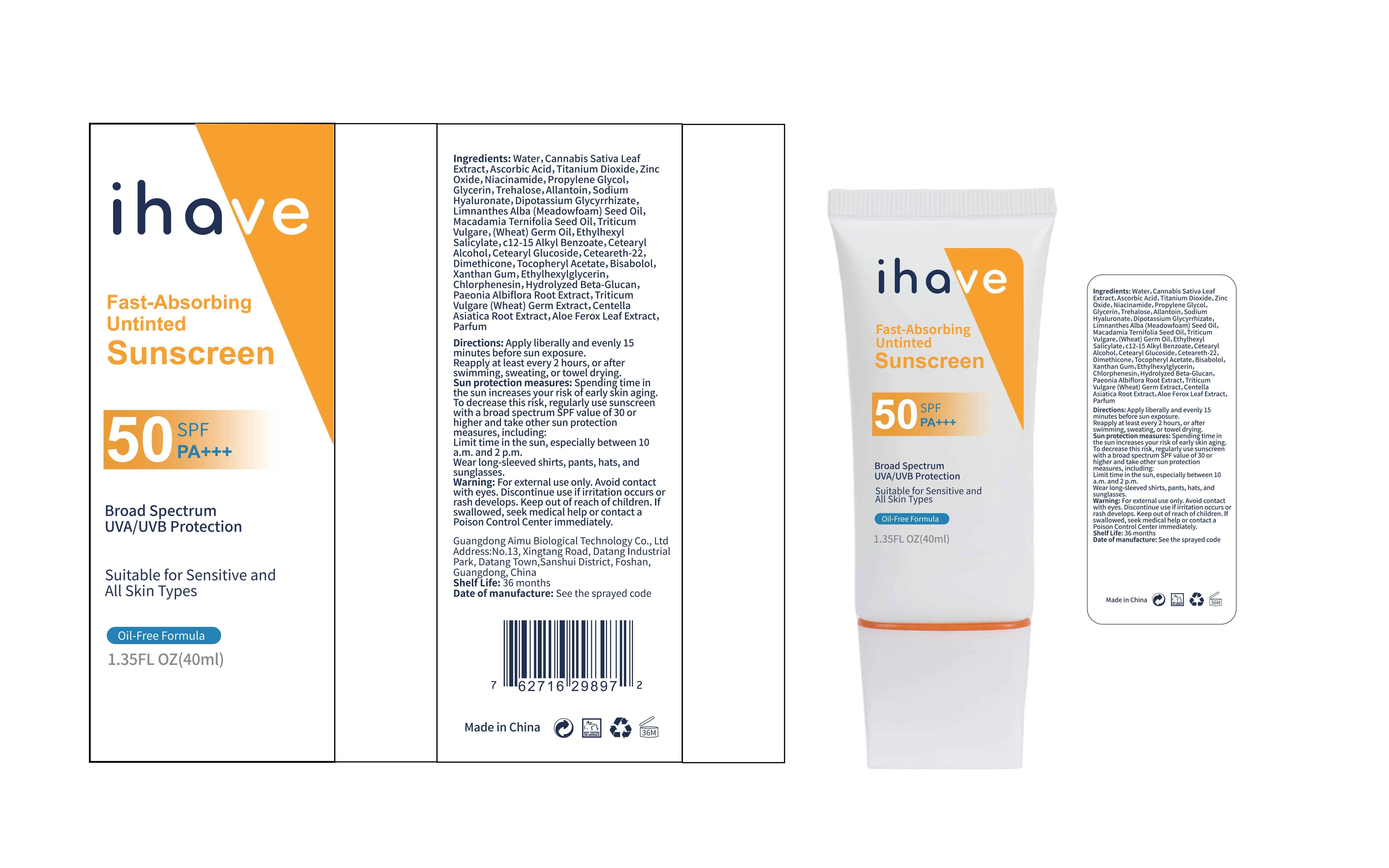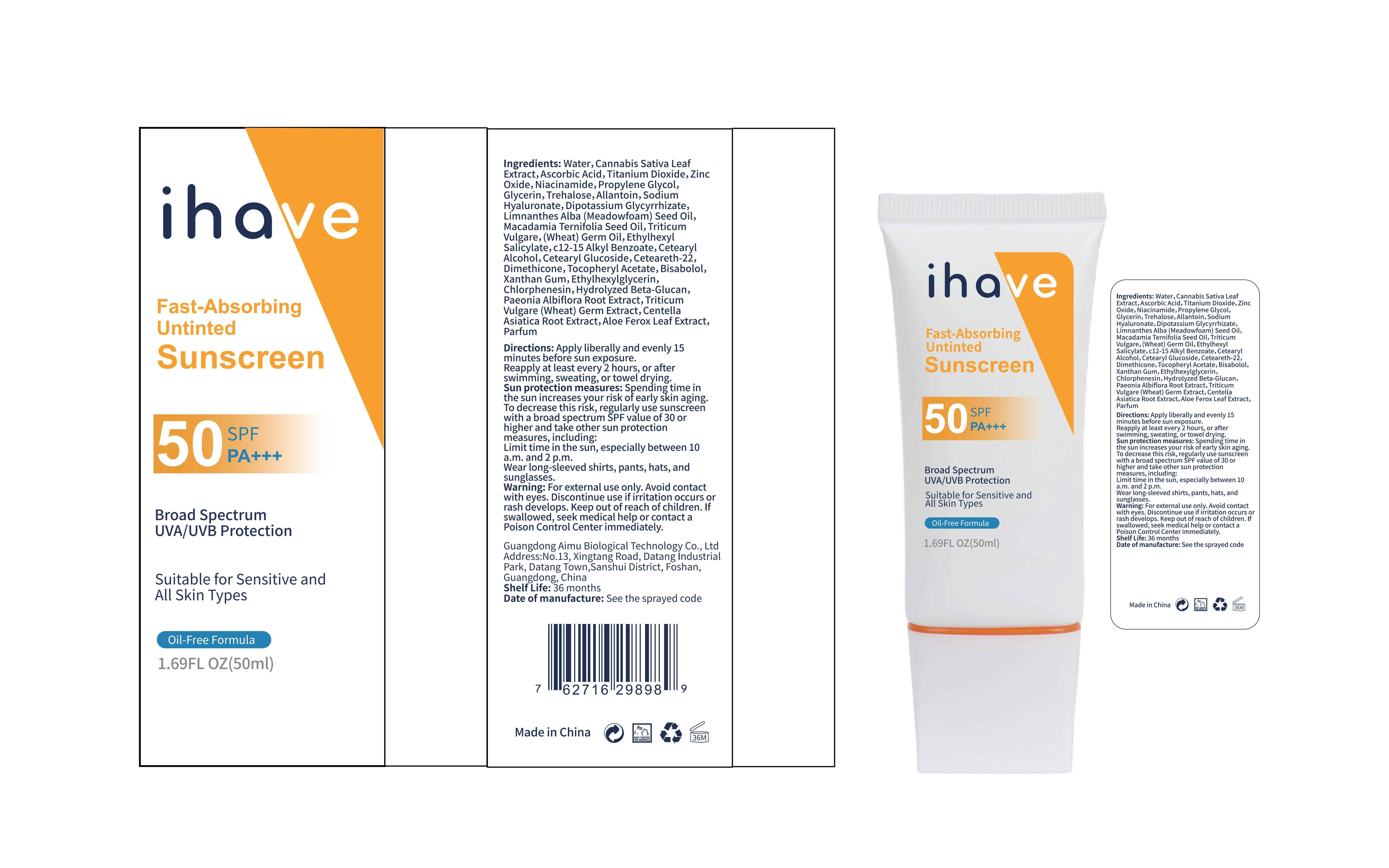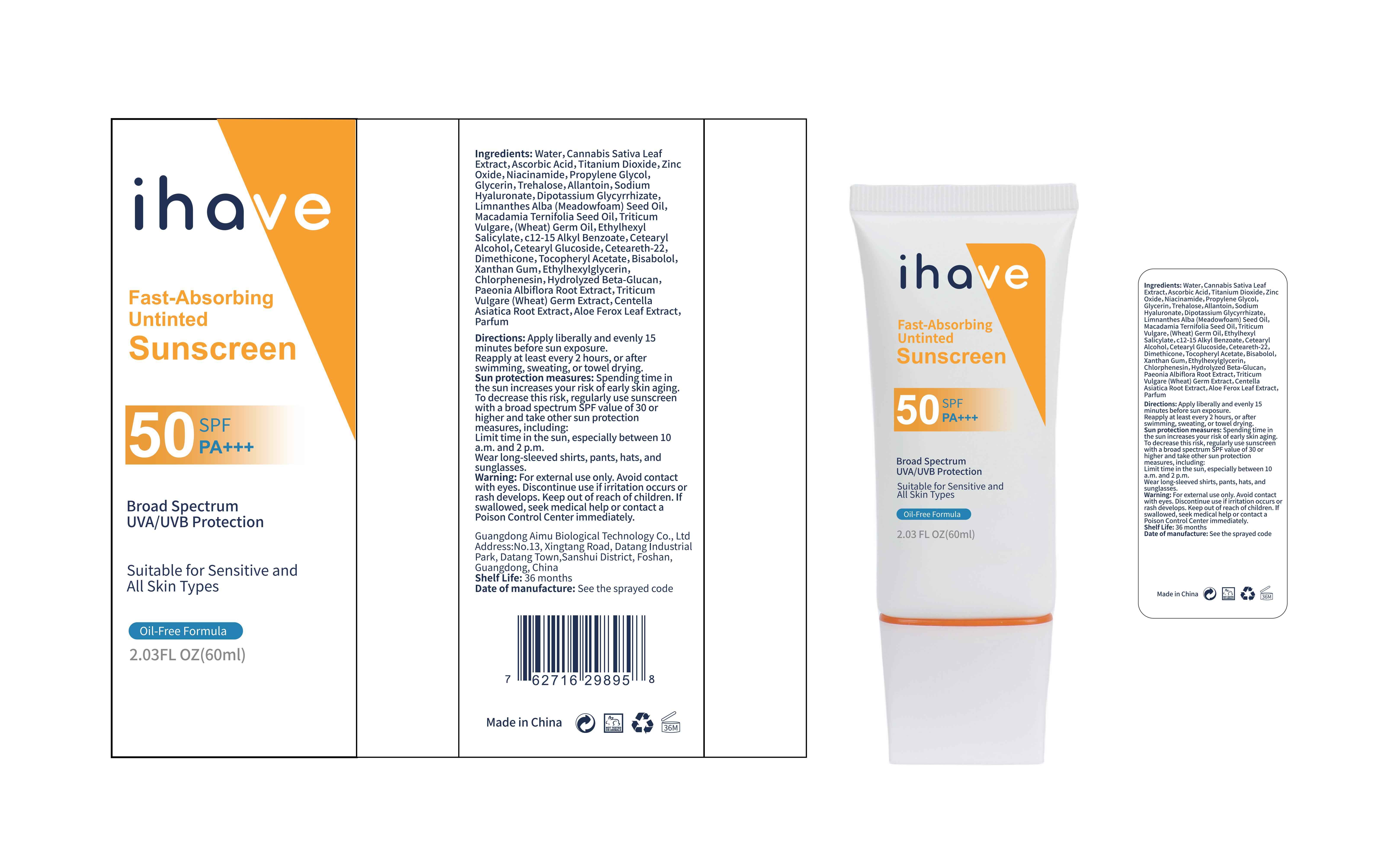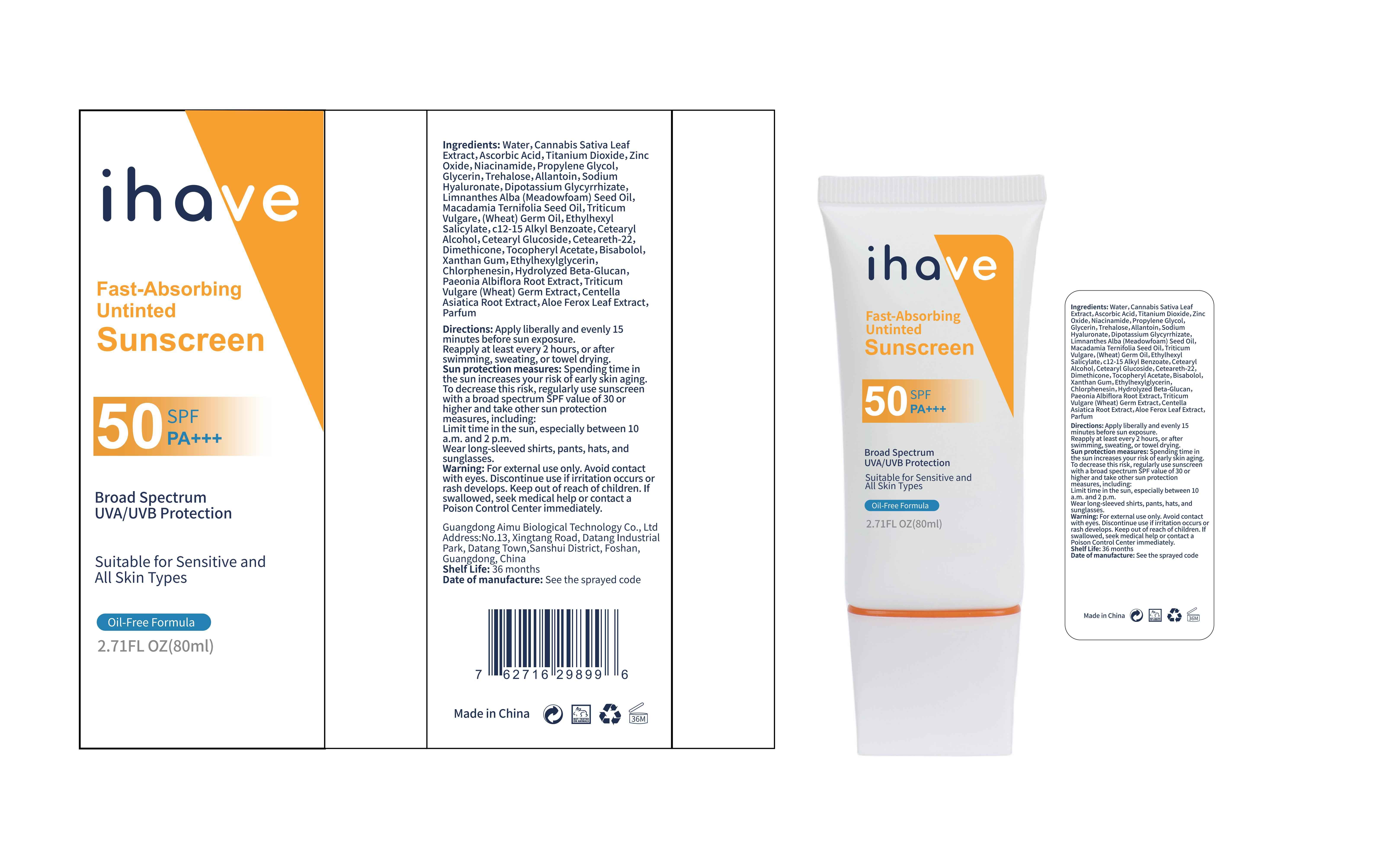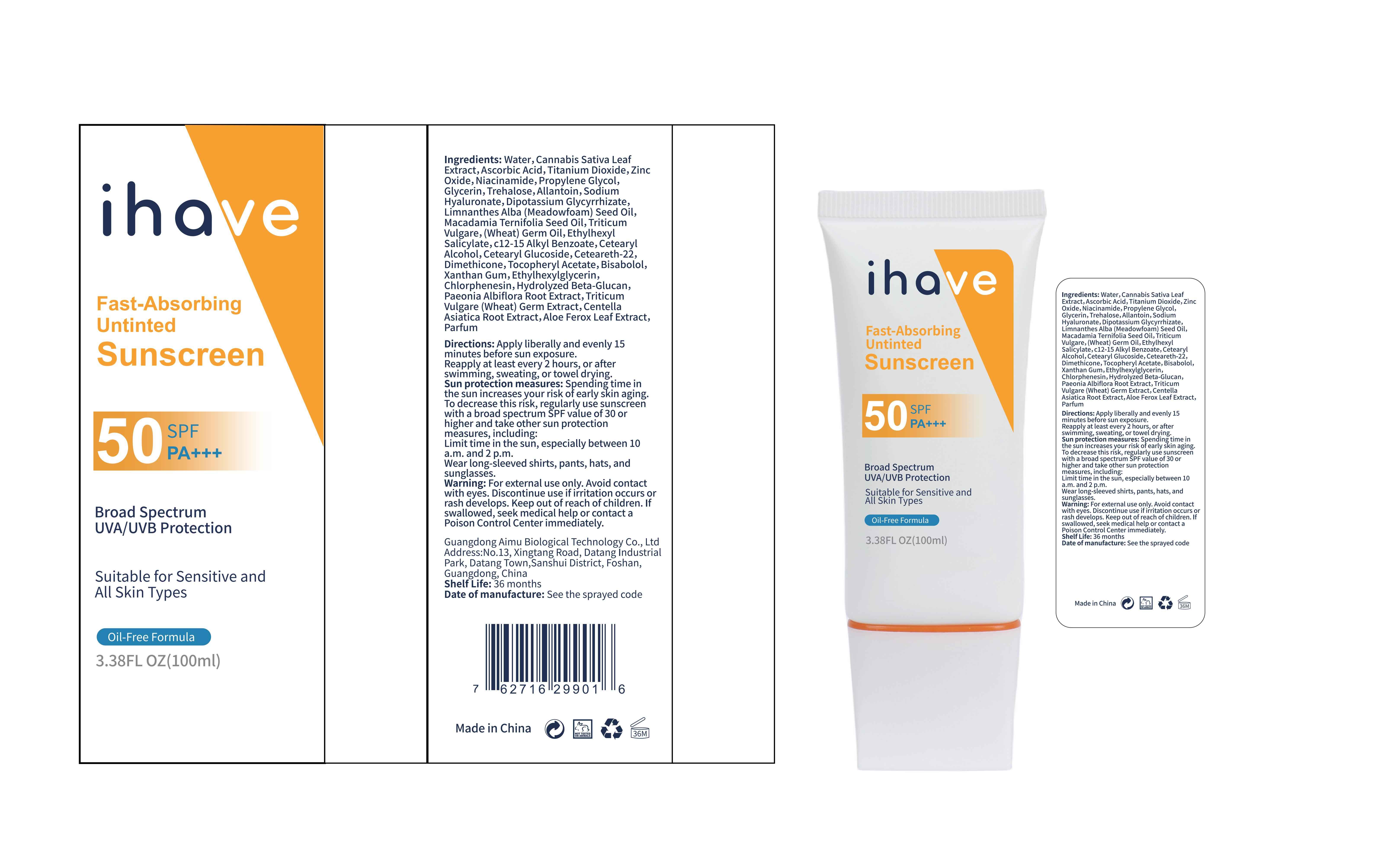 DRUG LABEL: ihave Sunscreen
NDC: 83566-501 | Form: CREAM
Manufacturer: Guangdong Aimu Biological Technology Co., Ltd
Category: otc | Type: HUMAN OTC DRUG LABEL
Date: 20240409

ACTIVE INGREDIENTS: TITANIUM DIOXIDE 6 g/100 mL; ZINC OXIDE 6 g/100 mL; OCTISALATE 3 g/100 mL
INACTIVE INGREDIENTS: GLYCERIN; TREHALOSE; ALLANTOIN; PAEONIA LACTIFLORA ROOT; CETEARYL GLUCOSIDE; CHLORPHENESIN; MEADOWFOAM SEED OIL; HYDROGENATED MACADAMIA SEED OIL; WHEAT GERM OIL; ASCORBIC ACID; CETEARETH-22; WATER; NIACINAMIDE; PROPYLENE GLYCOL; HYALURONATE SODIUM; DIMETHICONE; CANNABIS SATIVA LEAF; CETOSTEARYL ALCOHOL; ALPHA-TOCOPHEROL ACETATE; WHEAT GERM; GLYCYRRHIZINATE DIPOTASSIUM; ALKYL (C12-15) BENZOATE; ETHYLHEXYLGLYCERIN; 1,3-BETA-GLUCAN SYNTHASE COMPONENT FKS1; CENTELLA ASIATICA ROOT; ALOE FEROX LEAF; XANTHAN GUM; LEVOMENOL

ihave Sunscreen

ihave Sunscreen

ACTIVE INGREDIENT

TITANIUM DIOXIDE 6%, ZINC OXIDE 6%, ETHYLHEXYL SALICYLATE 3%

PURPOSE

Broad SpectrumUVA/UVB Protection

Keep out of reach of children.

INDICATIONS AND USAGE

Directions: Apply liberally and evenly 15minutes before sun exposure.Reapply at least every 2 hours, or afterswimming, sweating, or towel drying

WARNINGS

For external use only.

DOSAGE AND ADMINISTRATION

Directions: Apply liberally and evenly 15minutes before sun exposure.Reapply at least every 2 hours, or afterswimming, sweating,or towel drying

STORAGE AND HANDLING

Store in a dark and cool place

INACTIVE INGREDIENT

GLYCERIN
TREHALOSE
ALLANTOIN
PAEONIA LACTIFLORA ROOT
CETEARYL GLUCOSIDE
CHLORPHENESIN
MEADOWFOAM SEED OIL
HYDROGENATED MACADAMIA SEED OIL
WHEAT GERM OIL
ASCORBIC ACID
CETEARETH-22
WATER
NIACINAMIDE
PROPYLENE GLYCOL
HYALURONATE SODIUM
DIMETHICONE
CANNABIS SATIVA LEAF
CETOSTEARYL ALCOHOL
ALPHA-TOCOPHEROL ACETATE
WHEAT GERM
GLYCYRRHIZINATE DIPOTASSIUM
ALKYL (C12-15) BENZOATE
ETHYLHEXYLGLYCERIN
1,3-BETA-GLUCAN SYNTHASE COMPONENT FKS1
CENTELLA ASIATICA ROOT
ALOE FEROX LEAF
XANTHAN GUM
LEVOMENOL